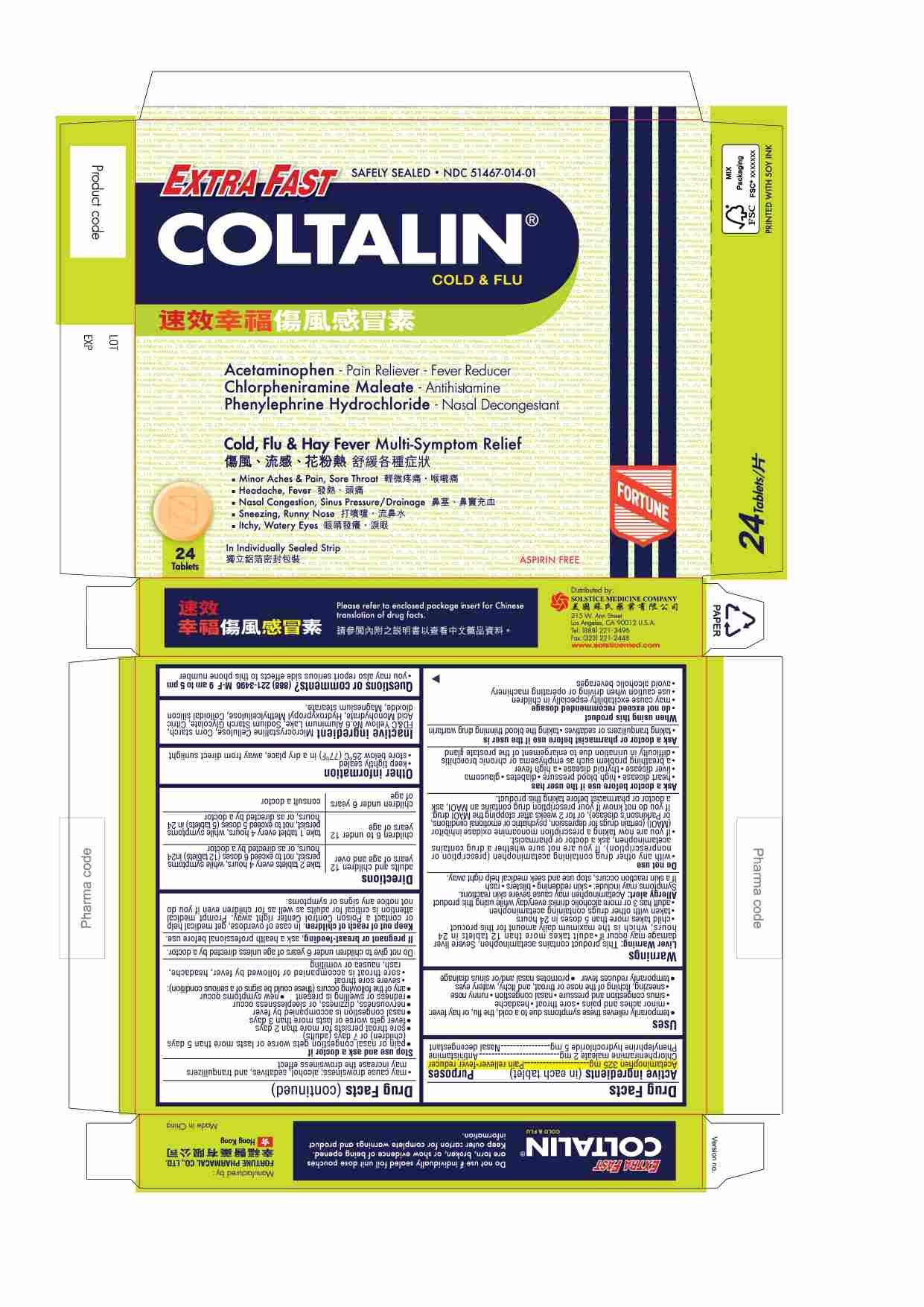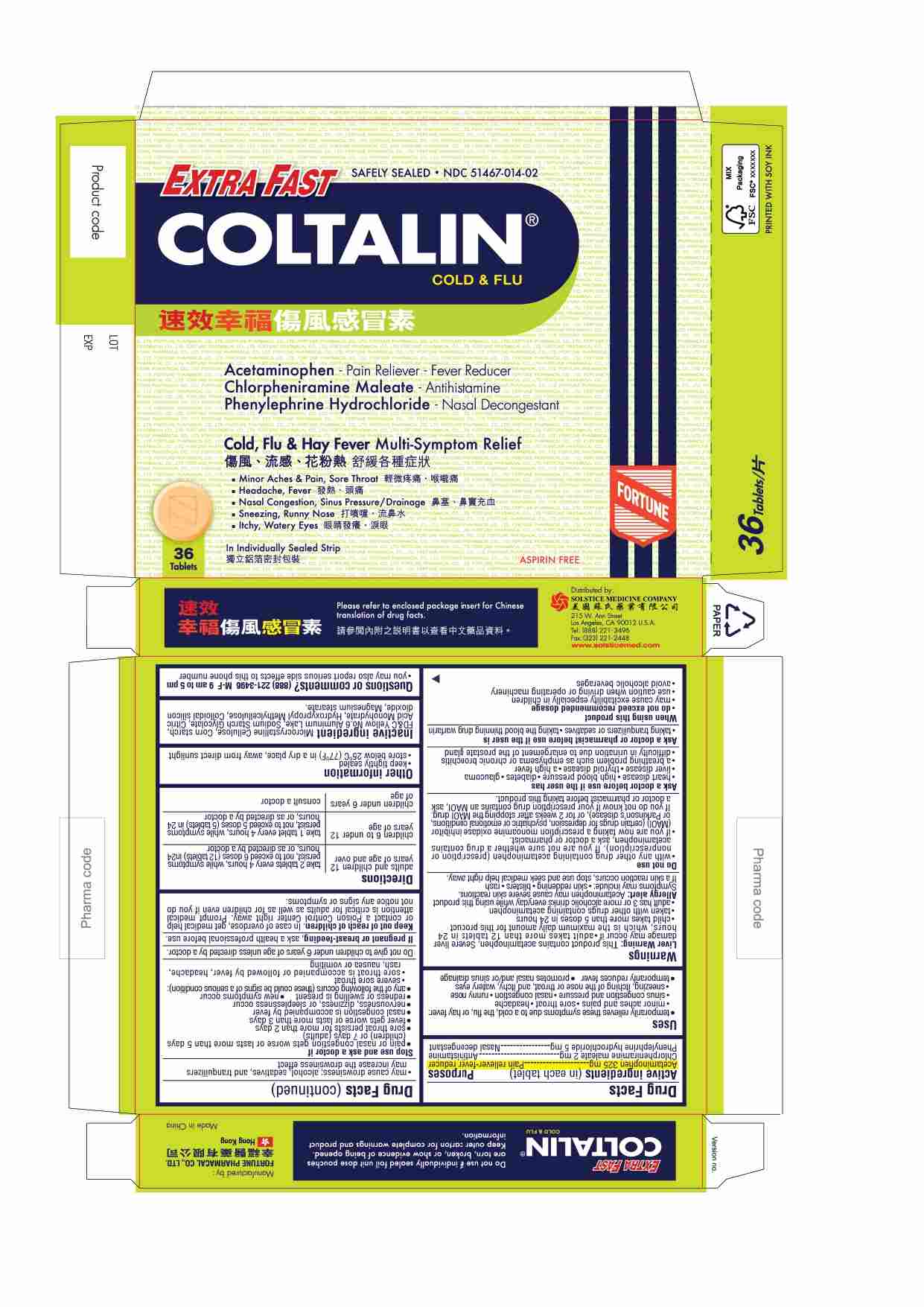 DRUG LABEL: EXTRA FAST COLTALIN
NDC: 51467-014 | Form: TABLET
Manufacturer: FORTUNE PHARMACAL COMPANY LIMITED
Category: otc | Type: HUMAN OTC DRUG LABEL
Date: 20260213

ACTIVE INGREDIENTS: ACETAMINOPHEN 325 mg/1 1; CHLORPHENIRAMINE MALEATE 2 mg/1 1; PHENYLEPHRINE HYDROCHLORIDE 5 mg/1 1
INACTIVE INGREDIENTS: SILICON DIOXIDE; STARCH, CORN; FD&C YELLOW NO. 6; MAGNESIUM STEARATE; SODIUM STARCH GLYCOLATE TYPE A POTATO; MICROCRYSTALLINE CELLULOSE; CITRIC ACID MONOHYDRATE; HYDROXYPROPYL METHYLCELLULOSE

Drug Facts

Active ingredients(in each tablet)
Acetaminophen 325 mg
Chlorpheniramine maleate 2 mg
Phenylephrine hydrochloride 5 mg

Purpose
Pain reliever-fever reducer
Antihistamine
Nasal decongestant

Uses
■ temporarily relieves these symptoms due to a cold, the flu, or hay fever:
■ minor aches and pains
■ sore throat
■ headache
■ runny nose
■ sinus congestion and pressure
■ nasal congestion due to a cold or hay fever
■ runny nose
■ sneezing, itching of the nose or throat, and itchy, watery eyes due to hay fever
■ temporarily reduces fever
■ promotes nasal and/or sinus drainage

Warnings

Liver Warning: This product contains acetaminophen. Severe liver damage may occur if

- adult takes more than 12 tablets in 24 hours, which is the maximum daily amount for this product
- child takes more than 5 doses in 24 hours
- taken with other drugs containing acetaminophen
- adult has 3 or more alcoholic drinks everyday while using this product

Allergy alert: Acetaminophen may cause severe skin reactions.

Symptoms may include:

- skin reddening
- blisters
- rash

If a skin rash occurs, stop use and seek medical help right away.

Do not use
■ with any other drug containing acetaminophen (prescription or nonprescription). If you are not sure whether a drug contains acetaminophen, ask a doctor or pharmacist.
■ if you are now taking a prescription monoamine oxidase inhibitor (MAOI) (certain drugs for depression, psychiatric or emotional conditions, or Parkinson’s disease), or for 2 weeks after stopping the MAOI drug. If you do not know whether a prescription drug contains an MAOI, ask a doctor or pharmacist before taking this product.

Ask a doctor before use if the user has
■ heart disease
■ high blood pressure
■ diabetes
■ glaucoma
■ liver disease
■ thyroid disease
■ a high fever
■ a breathing problem such as emphysema or chronic bronchitis
■ difficulty in urination due to enlargement of the prostate gland

Ask a doctor or pharmacist before use if the user is
■ taking tranquilizers or sedatives
■ taking the blood thinning drug warfarin

When using this product
■ do not exceed recommended dosage
■ may cause excitability especially in children
■ use caution when driving or operating machinery
■ avoid alcoholic beverages
■ may cause drowsiness; alcohol, sedatives, and tranquilizers may increase the drowsiness effect

Stop use and ask a doctor if
■ pain or nasal congestion gets worse or lasts more than 5 days (children) or 7 days (adults)
■ sore throat persists for more than 2 days
■ fever gets worse or lasts more than 3 days
■ nasal congestion is accompanied by fever
■ nervousness, dizziness, or sleeplessness occur
■ redness or swelling is present
■ new symptoms occur
■ any of the following occurs (these could be signs of a serious condition):
■ severe sore throat
■ sore throat is accompanied or followed by fever, headache, rash, nausea or vomiting

WARNINGS

Do not give to children under 6 years of age unless directed by doctor.

PREGNANCY OR BREAST FEEDING

If pregnant or breast-feeding,ask a health professional before use.

Keep out of reach of children.In case of overdose, get medical help or contact a Poison Control Center right away.
Prompt medical attention is critical for adults as well as children even if you do not notice any signs or symptoms.

Directions
■ adults and children 12 years of age and over: 2 tablets every 4 hours, while symptoms persist, not to exceed 6 doses (12 tablets) in 24 hours, or as directed by a doctor
■ children 6 to under 12 years of age: 1 tablet every 4 hours, while symptoms persist, not to exceed 5 doses (5 tablets) in 24 hours, or as directed by a doctor
■ children under 6 of age : consult a doctor

Other information
■ keep tightly sealed
■ store between below 25 C (77 F) in a dry place, away from direct sunlight

Inactive ingredients
Microcrystalline Cellulose, corn starch, FD&C yellow no. 6 aluminum lake, sodium starch glycolate, Citric Acid Monohydrate, Hydroxypropyl Methylcellulose, Colloidal silicon dioxide, magnesium stearate

Questions or comments? (888) 221-3496 M-F 9 am to 5 pm
■ you may also report serious side effects to this phone number

PACKAGE LABEL

EXTRA FAST COLTALIN

Safely Sealed

NDC 51467-014-01

Acetaminophen - Pain Reliever-Fever Reducer
Chlorpheniramine maleate - Antihistamine
Phenylephrine hydrochloride - Nasal Decongestant

Cold, Flu & Hay Fever Multi-Symptom Relief
■ Minor Aches & Pain, Sore Throat
■ Headache, Fever
■ Nasal Congestion, Sinus Pressure/Drainage
■ Sneezing, Runny Nose
■ Itchy, Watery Eyes

24 Tablets

In Individually Sealed Strip

Aspirin Free

PACKAGE LABEL

EXTRA FAST COLTALIN

Safely Sealed

NDC 51467-014-02

Acetaminophen - Pain Reliever-Fever Reducer
Chlorpheniramine maleate - Antihistamine
Phenylephrine hydrochloride - Nasal Decongestant

Cold, Flu & Hay Fever Multi-Symptom Relief
■ Minor Aches & Pain, Sore Throat
■ Headache, Fever
■ Nasal Congestion, Sinus Pressure/Drainage
■ Sneezing, Runny Nose
■ Itchy, Watery Eyes

36 Tablets

In Individually Sealed Strip

Aspirin Free